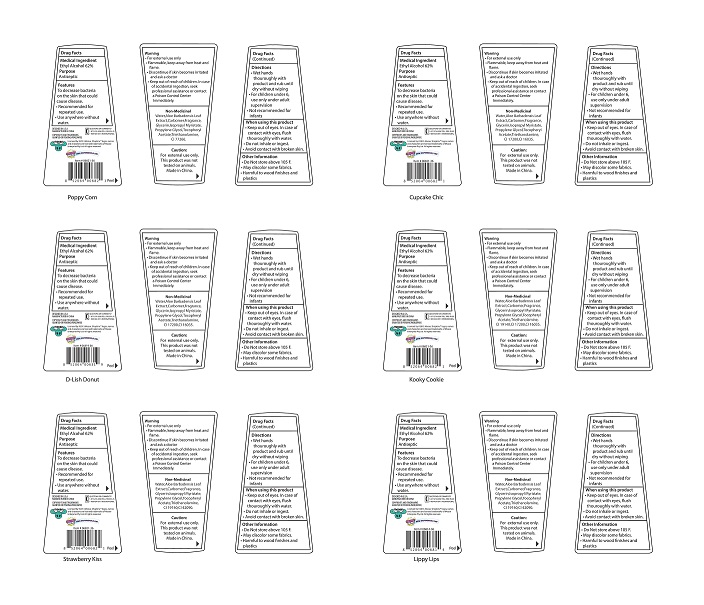 DRUG LABEL: Shopkins 3D Hand Sanitizer
NDC: 70108-006 | Form: GEL
Manufacturer: Ashtel Studios Inc.
Category: otc | Type: HUMAN OTC DRUG LABEL
Date: 20191231

ACTIVE INGREDIENTS: ALCOHOL 62 g/59 g
INACTIVE INGREDIENTS: SODIUM HYDROXIDE; WATER; PROPYLENE GLYCOL; CARBOMER HOMOPOLYMER TYPE C (ALLYL PENTAERYTHRITOL CROSSLINKED); TROLAMINE; GLYCERIN; ISOPROPYL MYRISTATE; .ALPHA.-TOCOPHEROL ACETATE

Shopkins 3D Hand Sanitizer

Use

To decrease bacteria on the skin that could cause disease.

Keep out of reach of children.

INDICATIONS AND USAGE

3D Hand Sanitizer

2 FL OZ (59mL)

Warnings

- for external use only-hands.
- keep out of eyes. avoid contact with broken skin.
- stop use and ask a Doctor if irritation or redness develops.
- do not inhale or ingest. if swallowed, get medical help or contact a poison control center right away.

Directions

- Wet hands thoroughly with product and rub without wiping
- Rub a dime sized drop into hands.
- For children under 6 use under adult supervision.
- Not recommended for infants

Inactive Ingredients

Water (aqua/eau)

Aloe Barbadensis Leaf Extract

Carbomer

Fragrance

Glycerin

Isopropyl Myristate

Proplyene Glycol

Tocopheryl Acetate

Trienthanolamine

Active Ingredient

Ethyl Alcohol 62%

Purpose: Antibacterial